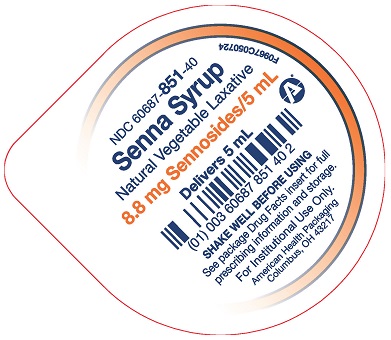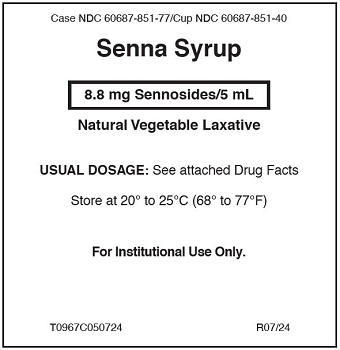 DRUG LABEL: Senna
NDC: 60687-851 | Form: LIQUID
Manufacturer: American Health Packaging
Category: otc | Type: HUMAN OTC DRUG LABEL
Date: 20260114

ACTIVE INGREDIENTS: SENNOSIDES 8.8 mg/5 mL
INACTIVE INGREDIENTS: PROPYLPARABEN; WATER; SUCROSE; CITRIC ACID ACETATE; GLYCERIN; METHYLPARABEN; POTASSIUM SORBATE

Senna Syrup
Drug Facts

Active ingredient

(per 5 mL cup)
Sennosides – 8.8 mg

Purpose

Laxative

Uses

- relieves occasional constipation (irregularity)
- generally causes bowel movement in 6 to 12 hours

Warnings

Do Not Use

- laxative products for longer than 1 week unless directed by a doctor.

Ask a doctor or pharmacist before use if you have

- stomach pain
- nausea
- vomiting
- noticed a change in bowel movement that continues over a period of 2 weeks

Stop use and ask a doctor if

you have rectal bleeding or failure to have a bowel movement after use of laxative. These may indicate a serious condition.

If pregnant or breast-feeding,

ask a health professional before use.

Keep out of reach of children.

In case of accidental overdose, get medical help or contact a Poison Control Center (1-800-222-1222) immediately.

Directions

- shake well before use
- Do not exceed recommended dose

Age | Starting Dose | Maximum dosage
Adults and children 12 years and older | 2 to 3 unit dose cups once a day preferably at bedtime; increase as needed or as recommended by a doctor | 3 unit dose cups in the morning and 3 unit dose cups at bedtime
Under 12 years of age | ask a doctor | ask a doctor

Other Information

- store at room temperature 20° to 25°C (68° to 77°F).
- a brown, natural flavored syrup supplied in the following oral dosage form:
  5 mL unit dose cups: 40 cups (4 x 10) NDC 60687-851-77

Inactive Ingredients

citric acid, glycerin, methylparaben, potassium sorbate, propylparaben, purified water, and sucrose.

Questions or comments?

Call 1-800-845-8210

Generic Section

DO NOT USE IF SEAL IS BROKEN.

Distributed by:
American Health Packaging
Columbus, OH 43217

R07/24

Principal Display Panel – Label – 8.8 mg/5 mL

Case NDC 60687-851-77/Cup NDC 60687-851-40

Senna Syrup

8.8 mg Sennosides/5 mL

Natural Vegetable Laxative

USUAL DOSAGE:See attached Drug Facts

Store at 20° to 25°C (68° to 77°F)

For Institutional Use Only.

T0967C050724 R07/24

Principal Display Panel – Cup Lid – 8.8 mg/5 mL

NDC 60687- 851-40

Senna Syrup
Natural Vegetable Laxative
8.8 mg Sennosides/5 mL
Delivers 5 mL

SHAKE WELL BEFORE USING

See package Drug Facts insert for full
prescribing information and storage.

For Institutional Use Only.

American Health Packaging
Columbus, OH 43217

F0967C050724